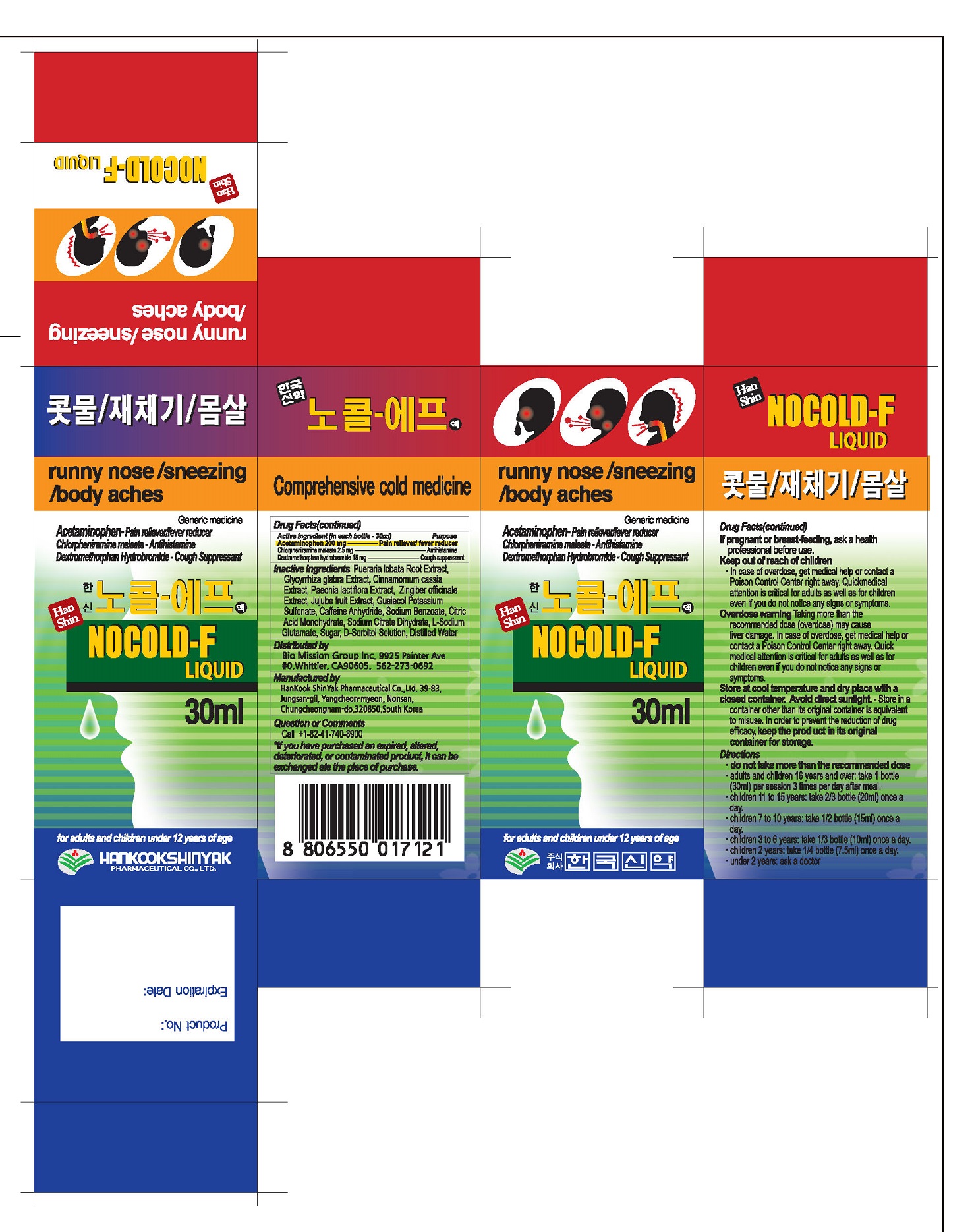 DRUG LABEL: NOCOLD-F
NDC: 72988-0027 | Form: LIQUID
Manufacturer: Lydia Co., Ltd.	
Category: otc | Type: HUMAN OTC DRUG LABEL
Date: 20211113

ACTIVE INGREDIENTS: ACETAMINOPHEN 200 mg/30 mL; DEXTROMETHORPHAN HYDROBROMIDE 15 mg/30 mL; CHLORPHENIRAMINE MALEATE 2.5 mg/30 mL
INACTIVE INGREDIENTS: SODIUM BENZOATE

ACTIVE INGREDIENT

ACETAMINOPHENE. CHLORPHENIRAMINE MALEATE, DEXTROMETHORPHAN HYDROBROMID

PURPOSE

First symtoms of a cold(snot, nasal stuffiness, sneeze, throat pain, cough, phlegm, chill, pyrexia, headache, arthralgia, myalgia) alleviate

Keep out of reach of children

INDICATIONS AND USAGE

adult and children 16 years and over: take 1 bottle per session 3 times a day after meal

children 11 to 15 years: take 2/3 bottle once a day

children 7 to 10 years: take 1/2 bottle once a day

children 3 to 6 years: take 1/3 bottle once a day

children 2 years: take 1/4 bottle once a day

under 2 years: ask a doctor

When using this product
Do not use for a period longer than 1 weeks
Stop use and ask a doctor if nervousness, dizziness, or sleepness occur. Pain, nasal congestion or cough gets worse or lasts more than 7 days.
fever gets worse or lasts more than 3 days
New symptoms occur
These may be signs of a serious condition.
If pregnant or breast-feeding, ask a health professional before use.
Keep out of reach of children, In case of overdose, get medical help or contact a poison control center right away

INACTIVE INGREDIENT

SODIUM BENZOATE, CITRIC ACID MONOHYDRATE,
SODIUM CITRATE DIHYDRATE, L-SODIUM GLUTAMATE, SUGAR,
D-SORBITOL SOLUTION, DISTILLED WATER

DOSAGE AND ADMINISTRATION

For oral use only